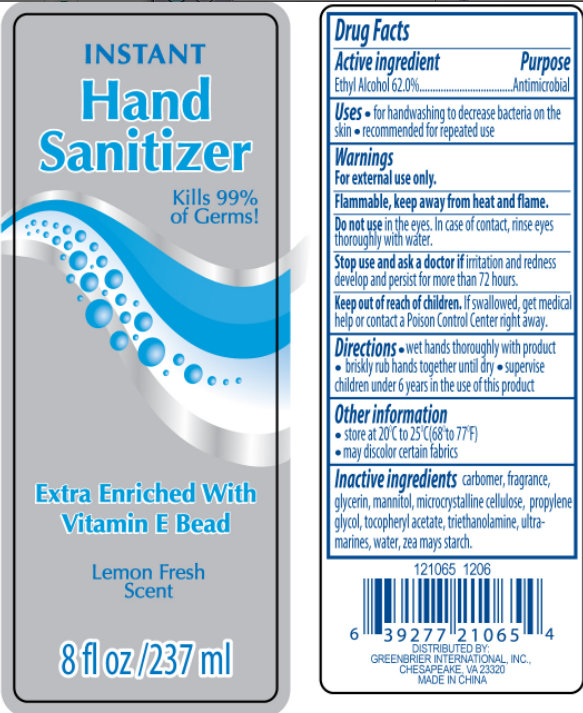 DRUG LABEL: INSTANT Hand Sanitizer Extra Enriched With Vitamin E Lemon Fresh Scent 
NDC: 33992-1062 | Form: GEL
Manufacturer: Greenbrier International, Inc.
Category: otc | Type: HUMAN OTC DRUG LABEL
Date: 20120510

ACTIVE INGREDIENTS: ALCOHOL 62 mL/100 mL
INACTIVE INGREDIENTS: GLYCERIN; MANNITOL; CELLULOSE, MICROCRYSTALLINE; ALPHA-TOCOPHEROL ACETATE; TROLAMINE; PROPYLENE GLYCOL; ULTRAMARINE BLUE; BARIUM CHROMATE; WATER; STARCH, CORN

INSTANT Hand Sanitizer Extra Enriched With Vitamin E Bead Lemon Fresh Scent

Active Ingredient

Ethyl Alcohol 62.0%

Purpose

Antimicrobial

Uses

- for handwashing to decrease bacteria on the skin
- recommended for repeated use

Warnings

For external use only.

Do not use

in the eyes. In case of contact, rinse eyes thoroughly with water.

Stop use and ask a doctor if

irritation and redness develop and persist for more than 72 hours.

Keep out of reach of children.

If swallowed, get medical help or contact a Poison Control Center right away.

Directions

- wet hands thoroughly with product
- briskly rub hands together until dry
- supervise children under 6 years in the use of this product

Other information

- store at 20 degrees C (68 to 77 degrees F).
- may discolor certain fabrics.

Inactive Ingredients

carbomer, fragrance, glycerin, mannitol, microcrystalline cellulose, propylene glycol, tocopheryl acetate, triethanolamine, ultramarines, water, zea mays starch.

DESCRIPTION

Distributed By: GREENBRIAR INTERNATIONAL, INC.,

CHESAPEAKE, VA 23320

MADE IN CHINA

PACKAGE LABEL

INSTANT

Hand Sanitizer

Kills 99.99 percent of Germs!

Extra Enriched With Vitamin E Bead

Lemon Fresh Scent

8 fl oz / 237 ml